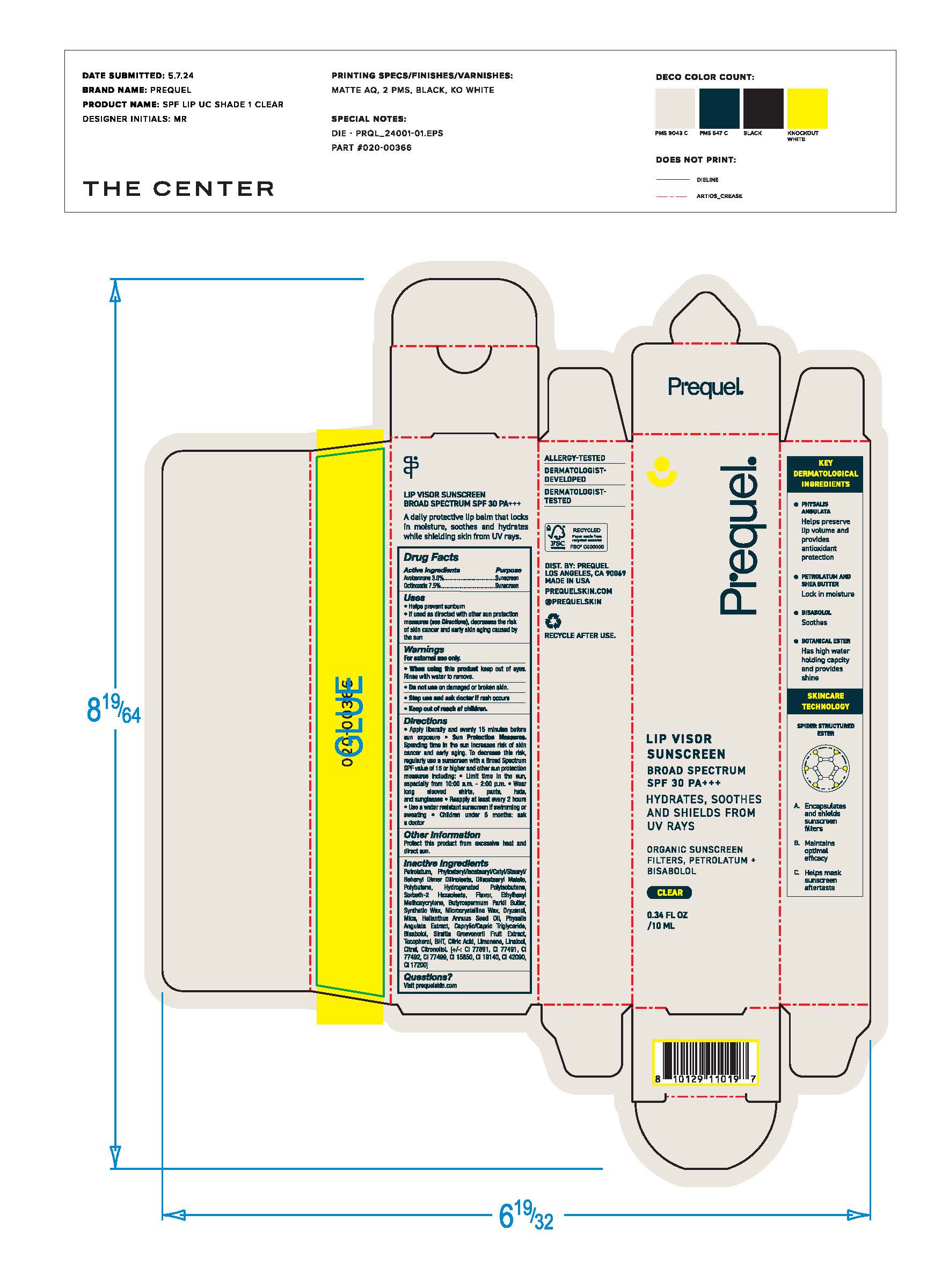 DRUG LABEL: Prequel Lip Visor SPF 30 ROSEDUST
NDC: 82800-080 | Form: LIQUID
Manufacturer: The Center Brands, LLC
Category: otc | Type: HUMAN OTC DRUG LABEL
Date: 20251204

ACTIVE INGREDIENTS: AVOBENZONE 3 mg/100 mg; OCTINOXATE 7.5 mg/100 mg
INACTIVE INGREDIENTS: DIISOSTEARYL MALATE; POLYBUTENE (1400 MW); HYDROGENATED POLYISOBUTENE (1300 MW); SORBETH-2 HEXAOLEATE; ETHYLHEXYL METHOXYCRYLENE; BUTYROSPERMUM PARKII (SHEA) BUTTER; SYNTHETIC WAX (1200 MW); MICROCRYSTALLINE WAX; ORYZANOL; MICA; HELIANTHUS ANNUUS (SUNFLOWER) SEED OIL; PHYSALIS ANGULATA WHOLE; CAPRYLIC/CAPRIC TRIGLYCERIDE; BISABOLOL; SIRAITIA GROSVENORII FRUIT; TOCOPHEROL; BHT; CITRIC ACID; LIMONENE, (+/-)-; LINALOOL, (+/-)-; CITRAL; CITRONELLOL; TITANIUM DIOXIDE; BROWN IRON OXIDE; FD&C BLUE NO. 1; YELLOW 5; RED 7; RED 33; PHYTOSTERYL/ISOSTEARYL/CETYL/STEARYL/BEHENYL DIMER DILINOLEATE; PETROLATUM

Prequel Lip Visor SPF 30 ROSEDUST

Active Ingredients

Avobenzone 3.0%

Octinoxate 7.5%

Uses

• helps prevent sunburn • if used as directed with other
sun protection measures (see Directions), decreases the
risk of skin cancer and early skin aging caused by the sun

Warnings

For external use only
Do not use on damaged or broken skin.
When using this product keep out of eyes. Rinse with water to remove.
Stop use and ask a docor if rash occurs
Keep out of reach of children.

Directions

• apply liberally and evenly 15 minutes before sun exposure
• reapply: •at least every 2 hours.

• use a water resistant sunscreen if swimming or sweating
• Sun Protection Measures. Spending time in the sun

increases your risk of skin cancer and early skin aging. To decrease
this risk, regularly use a sunscreen with a Broad Spectrum SPF
value of 15 or higher and other sun protection measures including:
• limit time in the sun, especially from 10 a.m. - 2 p.m.
• wear long-sleeved shirts, pants, hats, and sunglasses
• children under 6 months of age: Ask a doctor

Inactive ingredients

Petrolatum, Phytosteryl/Isostearyl/Cetyl/Stearyl/Behenyl Dimer Dilonleate, Diisostearyl Malate, Polybutene, Hydrogenated Polyisobutene, Sorbeth-2 Hexaoleate, Flavor, Ethylhexyl Methoxycrylene, Butyropsermum Parkii Butter, Synthetic Wax, Microcrystalline Wax, Oryzanol, Mica, Helianthus Annuus Seed Oil, Physalis Angulata Extract, Caprylic/Capric Triglyceride, Bisabolol, Siraita Grosvenorii Fruit Extract, Tocopherol, BHT, Citric Acid, Limonene, Linalool, Citral, Citronellol. [+/-: CI 77891, CI 77491, CI 77492, CI 77499, CI 15850, CI 19140, CI 42090, CI 17200]

Other Information

• protect the product from excessive heat and direct sun

Questions?

Visit prequelskin.com

Keep out of reach of children

Purpose

Sunscreen